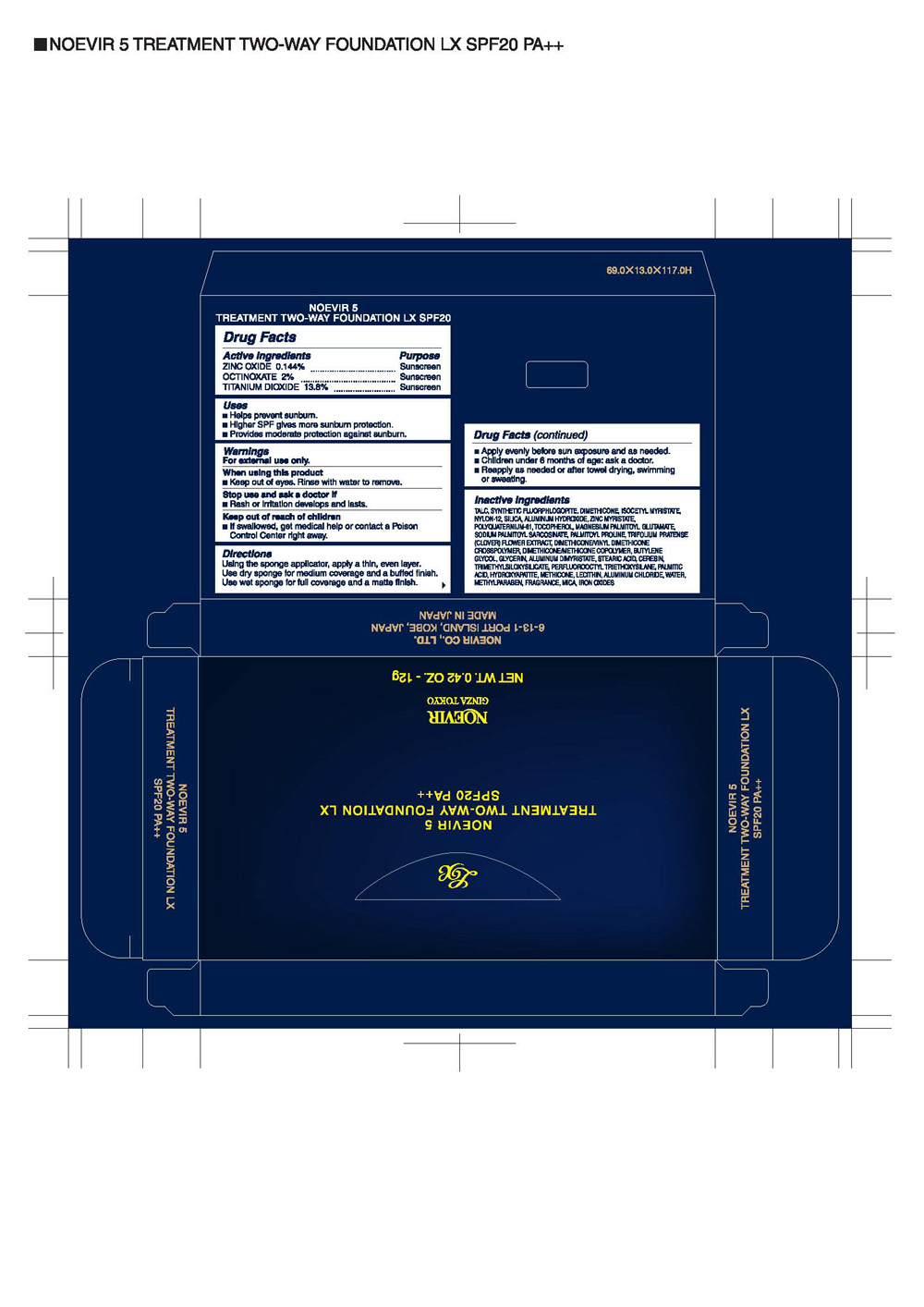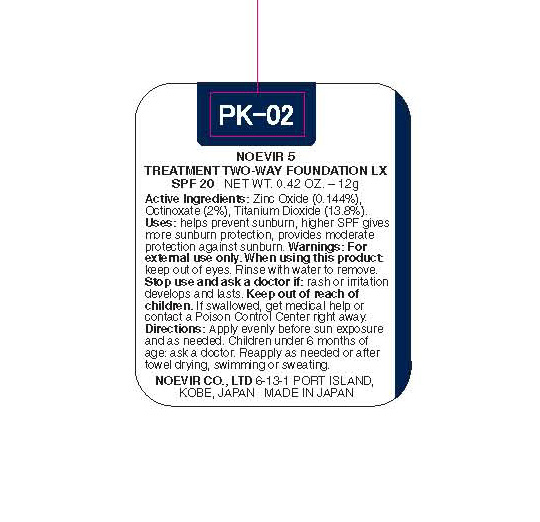 DRUG LABEL: NOEVIR N5
NDC: 62908-012 | Form: POWDER
Manufacturer: NOEVIR USA INC
Category: otc | Type: HUMAN OTC DRUG LABEL
Date: 20091208

ACTIVE INGREDIENTS: ZINC OXIDE 144 mg/100 g; OCTINOXATE 2000 mg/100 g; TITANIUM DIOXIDE 13800 mg/100 g

Drug Facts

Drug Facts

Active Ingredients Purpose
ZINC OXIDE 14.25% Sunscreen
OCTINOXATE 7.5% Sunscreen
TITANIUM DIOXIDE 2.07% Sunscreen
Uses

- Helps prevent sunburn.
- Higher SPF gives more sunburn protection.
- Provides high protection against sunburn.

Warnings
For external use only.
When using this product

- Keep out of eyes. Rinse with water to remove.

Stop use and ask a doctor if

- Rash or irritation develops and lasts.

Keep out of reach of children

- If swallowed, get medical help or contact a Poison Control Center right away.

Directions

- Apply evenly before sun exposure.
- Children under 6 months of age ask a doctor.
- Reapply as needed or after towel drying, swimming or sweating.

Other Information
Sun Alert
Limiting sun exposure, wearing protective clothing and using sunscreens may reduce the risks of skin aging, skin cancer, and other harmful effects of the sun.